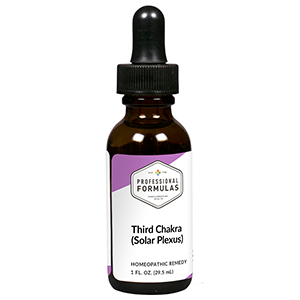 DRUG LABEL: Third Chakra (Solar Plexus)
NDC: 63083-7303 | Form: LIQUID
Manufacturer: Professional Complementary Health Formulas
Category: homeopathic | Type: HUMAN OTC DRUG LABEL
Date: 20190815

ACTIVE INGREDIENTS: AMARYLLIS BELLADONNA WHOLE 8 [hp_X]/29.5 mL; CALCIUM SULFATE ANHYDROUS 8 [hp_X]/29.5 mL; POTASSIUM CHLORATE 8 [hp_X]/29.5 mL; SODIUM PHOSPHATE, DIBASIC, HEPTAHYDRATE 8 [hp_X]/29.5 mL; STRYCHNOS NUX-VOMICA SEED 8 [hp_X]/29.5 mL; CINCHONA OFFICINALIS BARK 10 [hp_X]/29.5 mL; BUFO BUFO CUTANEOUS GLAND 12 [hp_X]/29.5 mL; FORMICA RUFA 12 [hp_X]/29.5 mL; LACHESIS MUTA VENOM 12 [hp_X]/29.5 mL; FERRIC OXIDE RED 30 [hp_X]/29.5 mL; SILICON DIOXIDE 30 [hp_X]/29.5 mL
INACTIVE INGREDIENTS: ALCOHOL; WATER

RCT3

ACTIVE INGREDIENTS

Belladonna 8X
Calcarea sulphurica 8X
Kali chloricum 8X
Natrum phosphoricum 8X
Nux vomica 8X
Cinchona officinalis 10X
Bufo rana 12X
Formica rufa 12X
Lachesis mutus 12X
Garnierite 30X, 60X, 100X
Hematite 30X, 60X, 100X
Rose quartz 30X, 60X, 100X

QUESTIONS

Professional Formulas

PO Box 2034 Lake Oswego, OR 97035

INDICATIONS

Temporarily relieves self-doubt, mistrust of family or friends, feeling powerless or ineffective, low self-esteem, anxiousness, being overly judgmental, or anger.*

PURPOSE

*Claims based on traditional homeopathic practice, not accepted medical evidence. Not FDA evaluated.

WARNINGS

In case of overdose, get medical help or contact a poison control center right away.

Keep out of the reach of children.

PREGNANCY OR BREAST FEEDING

If pregnant or breastfeeding, ask a healthcare professional before use.

DIRECTIONS

Place drops under tongue 30 minutes before/after meals. Adults and children 12 years and over: Take 5 drops up to 4 times per day for up to one month. Consult a physician for use in children under 12 years of age.

OTHER INFORMATION

Tamper resistant. If seal is broken, do not use. After opening, close container tightly and store at room temperature away from heat.

INACTIVE INGREDIENTS

20% ethanol, purified water.

LABEL

Est 1985

Professional Formulas

Complementary Health

Third Chakra (Solar Plexus)

Homeopathic Remedy

1 FL. OZ. (29.5 mL)